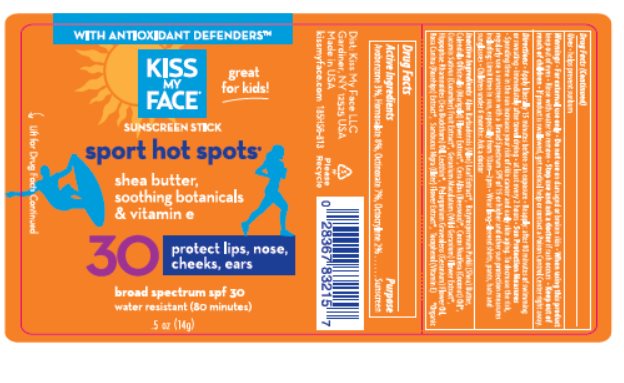 DRUG LABEL: Kiss My Face SPF 30 Face Stick
NDC: 65364-223 | Form: STICK
Manufacturer: Kiss My Face
Category: otc | Type: HUMAN OTC DRUG LABEL
Date: 20150518

ACTIVE INGREDIENTS: OCTINOXATE 7.0 mg/1 g; OCTOCRYLENE 2 mg/1 g; AVOBENZONE 3.0 mg/1 g; HOMOSALATE 8.0 mg/1 g
INACTIVE INGREDIENTS: COCONUT OIL 38 mg/1 g; WHITE WAX 37.5 mg/1 g; LECITHIN, SUNFLOWER 2.0 mg/1 g; .ALPHA.-TOCOPHEROL ACETATE 1.20 mg/1 g; SHEA BUTTER .1 mg/1 g

Drug Facts

Active ingredient

Avobenzone (3.0%), Homosalate (8.0%), Octinoxate (7.0%), Octocrylene (2.0%)

Purpose

Sunscreen

Keep Out of Reach of Children

If swallowed get medical help or contact a Poison Control Center right away.

Uses

Helps prevent sunburn.

Warnings

For external use only. Do not use on damaged or broken skin. When using this product keep out of eyes. Rinse with water to remove. Stop use and ask a doctor if rash occurs.

Directions

Apply liberally 15 minutes before sun exposure. Reapply: after 80 minutes of swimming or sweating, immediately after towel drying, at least every 2 hours. Sun Protection Measures: Spending time in the sun increases your risk of skin cancer and early skin aging. To decrease the risk, regularly use a sunscreen with a Broad Spectrum SPF of 15 or higher and other sun protection measures including: Limit time in the sun, especially from 10 AM – 2 PM . Wear long-sleeved shirts, pants, hats and sunglasses. Children under 6 months: Ask a doctor.

Inactive Ingredients

Aloe Barbadensis Leaf Extract*, Butyrospermum Parkii (Shea Butter), Calendula Officinalis Flower Extract*, Beeswax*, Cocos Nucifera (Coconut) Oil*, Cucumis Sativus (Cucumber) Fruit Extract*, Geranium Maculatum Extract*, Hippophae Rhamnoides Oil, Lecithin*, Pelargonium Graveolens Flower Oil Rosa Canina, Extract*,Sambucus Nigra Flower Extract*,

Tocophero.*Organic